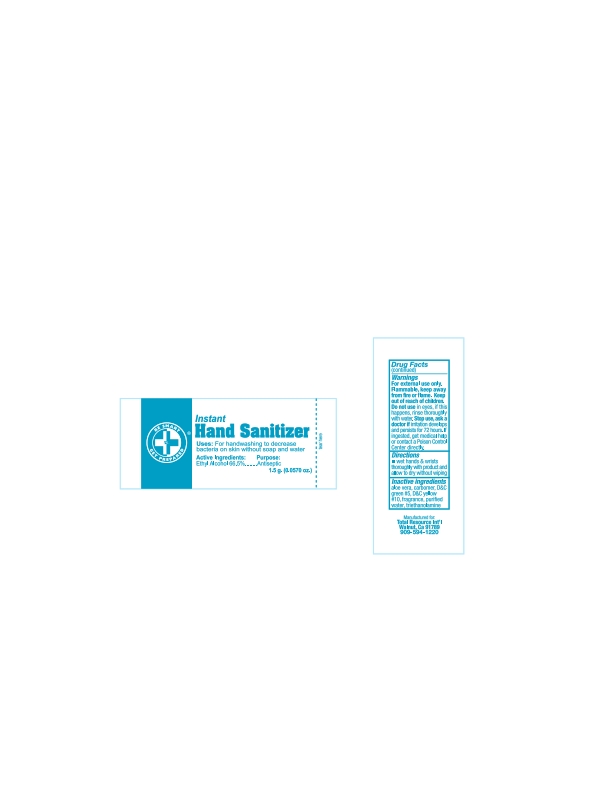 DRUG LABEL: HAND SANITIZER
NDC: 55550-108 | Form: PATCH
Manufacturer: Total Resources International Inc.
Category: otc | Type: HUMAN OTC DRUG LABEL
Date: 20221206

ACTIVE INGREDIENTS: ALCOHOL 66.5 mL/100 mL
INACTIVE INGREDIENTS: ALOE; TROLAMINE; WATER

Hand Sanitizer

Active ingredient Purpose

Ethyl Alcohol 66.5% v/v....................Antiseptic

PURPOSE

Use: For handwashing to decrease bacteria on skin without soap and water.

Warnings For external use only

Flammable, keep away from fire or flame

Do not use •in the eyes if happens, rinse thoroughly with water.

Stop use, ask a doctor if irritation develops and persists for 72 hours.

Keep out of reach of children. If swallowed, seek medical help or contact a Poison Control Center immediately.

INDICATIONS AND USAGE

Directions wet hands and wrists thoroughly with product and allow to dry without wiping supervise children while using this product

Other Information store at room temperature 59°- 86°F (15°- 30°C)

Inactive ingredient aloe vera*, carbomer*, D&C green #5*, D&C yellow #10*, fragrance *, triethanolamine*, water* may contain

Questions? Call 1-888-771-7824

DOSAGE AND ADMINISTRATION

For External Use Only